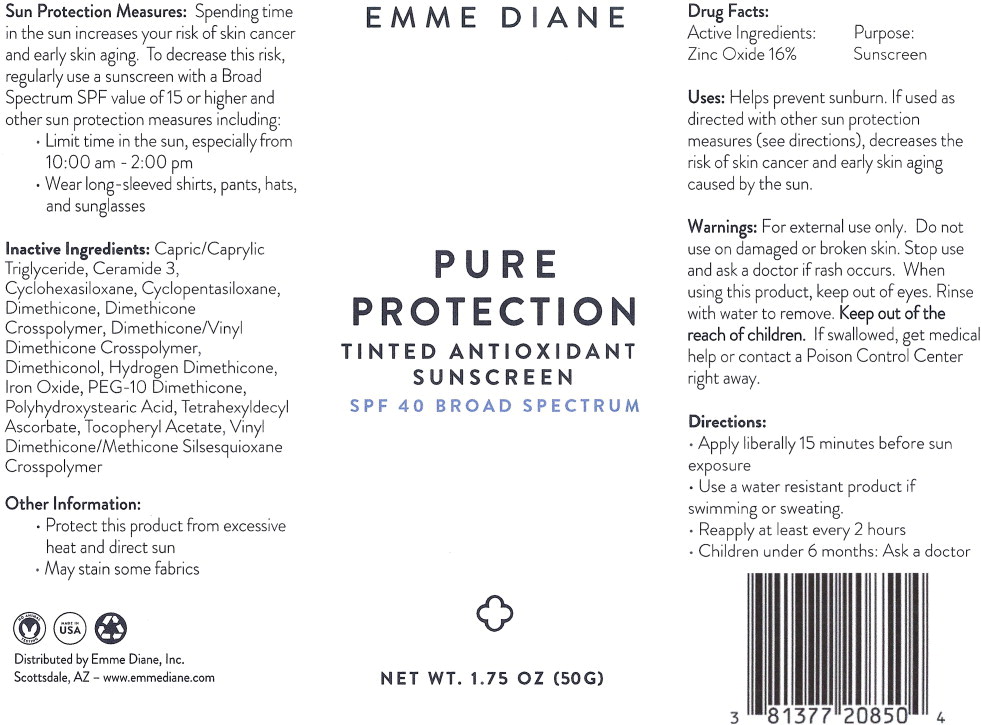 DRUG LABEL: Emme Diane Pure Protection Tinted Antioxidant Sunscreen
NDC: 81377-208 | Form: CREAM
Manufacturer: Emme Diane, Inc.
Category: otc | Type: HUMAN OTC DRUG LABEL
Date: 20250116

ACTIVE INGREDIENTS: Zinc Oxide 160 mg/1 g
INACTIVE INGREDIENTS: MEDIUM-CHAIN TRIGLYCERIDES; CERAMIDE NP; Cyclomethicone 6; Cyclomethicone 5; Dimethicone 20; Dimethicone Crosspolymer (450000 MPA.S AT 12% in Cyclopentasiloxane); Dimethicone/Vinyl Dimethicone Crosspolymer (Soft Particle); Dimethiconol (2000 CST); Brown Iron Oxide; Hydrogen Dimethicone (20 CST); PEG-10 Dimethicone (600 CST); POLYHYDROXYSTEARIC ACID (2300 MW); TETRAHEXYLDECYL ASCORBATE; .ALPHA.-TOCOPHEROL ACETATE; VINYL DIMETHICONE/METHICONE SILSESQUIOXANE CROSSPOLYMER

Drug Facts:

Active Ingredients:

Zinc Oxide 16%

Purpose:

Sunscreen

Uses:

Helps prevent sunburn. If used as directed with other sun protection measures (see directions), decreases the risk of skin cancer and early skin aging caused by the sun.

Warnings:

For external use only.

Do not use on damaged or broken skin.

Stop use and ask a doctor if rash occurs.

When using this product, keep out of eyes. Rinse with water to remove.

KEEP OUT OF REACH OF CHILDREN

Keep out of the reach of children. If swallowed, get medical help or contact a Poison Control Center right away.

Directions:

- Apply liberally 15 minutes before sun exposure
- Use a water resistant product if swimming or sweating.
- Reapply at least every 2 hours
- Children under 6 months: Ask a doctor

Sun Protection Measures: Spending time in the sun increases your risk of skin cancer and early skin aging. To decrease this risk, regularly use a sunscreen with a Broad Spectrum SPF value of 15 or higher and other sun protection measures including:

- Limit time in the sun, especially from 10:00 am-2:00 pm
- Wear long-sleeved shirts, pants, hats, and sunglasses

Inactive Ingredients:

Capric/Caprylic Triglyceride, Ceramide 3, Cyclohexasiloxane, Cyclopentasiloxane, Dimethicone, Dimethicone Crosspolymer, Dimethicone/Vinyl Dimethicone Crosspolymer, Dimethiconol, Hydrogen Dimethicone, Iron Oxide, PEG-10 Dimethicone, Polyhydroxystearic Acid, Tetrahexyldecyl Ascorbate, Tocopheryl Acetate, Vinyl Dimethicone/Methicone Silsesquioxane Crosspolymer

Other Information:

- Protect this product from excessive heat and direct sun
- May stain some fabrics

Principal Display Panel – 50 g Bottle Label

EMME DIANE

PURE
PROTECTION
TINTED ANTIOXIDANT
SUNSCREEN

SPF 40 BROAD SPECTRUM

NET WT. 1.75 OZ (50 G)